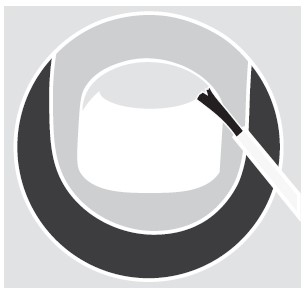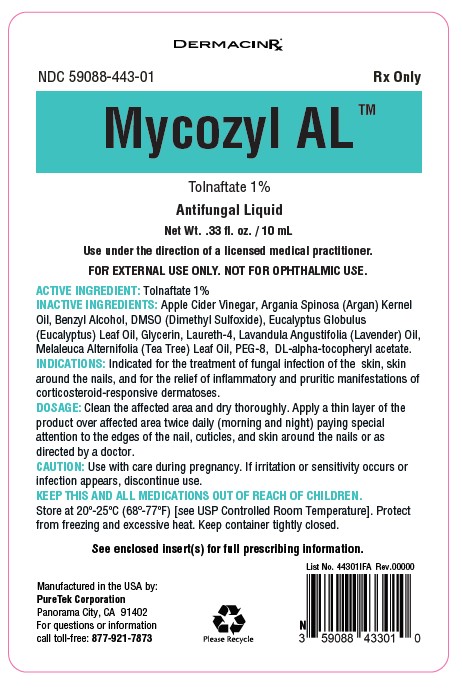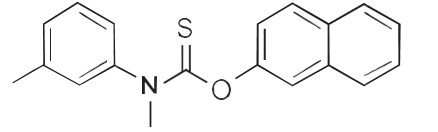 DRUG LABEL: Mycozyl AL
NDC: 59088-443 | Form: LIQUID
Manufacturer: PURETEK CORPORATION
Category: prescription | Type: HUMAN PRESCRIPTION DRUG LABEL
Date: 20231017

ACTIVE INGREDIENTS: TOLNAFTATE 0.1 g/10 mL
INACTIVE INGREDIENTS: .ALPHA.-TOCOPHEROL ACETATE, DL-; POLYETHYLENE GLYCOL 400; TEA TREE OIL; GLYCERIN; DIMETHYL SULFOXIDE; BENZYL ALCOHOL; LAURETH-4; APPLE CIDER VINEGAR; EUCALYPTUS OIL; ARGAN OIL; LAVENDER OIL

Mycozyl AL

DESCRIPTION:

Each gram of Mycozyl AL™ contains 10 mg of tolnaftate in a vehicle consisting of: Apple Cider Vinegar, Argania
Spinosa (Argan) Kernel Oil, Benzyl Alcohol, DMSO (Dimethyl Sulfoxide), Eucalyptus Globulus (Eucalyptus) Leaf
Oil, Glycerin, Laureth-4, Lavandula Angustifolia (Lavender) Oil, Melaleuca Alternifolia (Tea Tree) Leaf Oil, PEG-8,
DL-alpha-tocopheryl Acetate.

Chemically, tolnaftate molecular formula is C19H17NOS and molecular weight 314.5 and is represented by the
following structure formula:

CLINICAL PHARMACOLOGY:

Tolnaftate has antifungal properties.

Pharmacokinetics:

Tolnaftate is only given topically, and there are no documented reports on its pharmacokinetics and systemic metabolism.

INDICATIONS AND USAGE:

Mycozyl AL™ is effective in the treatment of most skin infections such as athlete's foot (tinea pedis) and ringworm (tinea corporis). Mycozyl AL™ has been designed to reach skin areas around and under the nails while it relives burning, cracking, scaling and discomfort which accompany these conditions. Mycozyl AL™ is an antifungal that works by preventing and eliminating the growth of fungus on fingers, toes and around the nails. It eliminates and helps stop the spread of fungal infections on cuticles around nail edges and under the nail tips where reachable with applicator brush. Mycozyl AL™ cures and prevents fungal infections from coming back with daily use.

CONTRAINDICATIONS:

Tolnaftate topically applied is not likely to affect drugs taken or injected, but many drugs can interact with each other.

PRECAUTIONS:

Keep out of reach of children. If swallowed, get medical help or contact a Poison Control Center right away. Avoid contact with eyes, lips and mucous membranes.

WARNINGS:

For External Use Only. Not For Ophthalmic Use

General:

Do not start, stop, or change the dosage of any medicine before checking with your doctor, health care provider or pharmacist first.

Carcinogenesis, Mutagenesis, and Impairment of Fertility:

Long-term animal studies have not been performed to evaluate the carcinogenic potential or the effect on fertility of Tolnaftate.

Pregnancy:

Teratogenic effects - There is currently no published human data available on the teratogenic and fetotoxic effects of tolnaftate.

Nursing Mothers:

Before using this medication while breastfeeding, it is recommended to consult with a healthcare professional.

Pediatric Use:

Safety and effectiveness have not been established in pediatric patients less than 2 years of age.

ADVERSE REACTIONS:

For athlete’s foot and ringworm - if irritation occurs or there is no improvement within 4 weeks.
For prevention of athlete’s foot – if irritation occurs, discontinue use and consult a doctor.

OVERDOSAGE:

(See PRECAUTIONS).

DOSAGE AND ADMINISTRATION:

• Clean the affected area with soap and warm water and dry thoroughly
• Apply a thin layer of product over affected area twice daily (morning and night) paying special attention to the edges of the nail, cuticles and skin around the nails or as directed by a doctor
• The brush applicator allows for easy application on skin around the nail and cuticle areas.
• For athlete's foot, pay special attention to spaces between the toes, wear well-fitting,ventilated shoes, and change shoes and socks at least once daily.
• For athlete's foot and ringworm, use daily for 4 weeks.
• Supervise children in the use of this product.

Use under the direction of a licensed medical practitioner.
Call your doctor about side effects. To report side effects, call PureTek Corporation at
1-877-921-7873 or FDA at 1-800-FDA-1088 or www.fda.gov/medwatch.

HOW SUPPLIED:

Mycozyl AL™ is supplied in:
10 mL glass bottle with a screw cap fitted with a brush applicator (NDC 59088-443-01).

Store at 20º-25ºC (68º-77ºF) [see USP Controlled Room Temperature]. Protect from freezing and excessive heat. Keep
container tightly closed.
Do not use if package is damaged. Keep out of reach of children.

Manufactured by:
PureTek Corporation
Panorama City, CA 91402
For questions or information
call toll-free: 877-921-7873